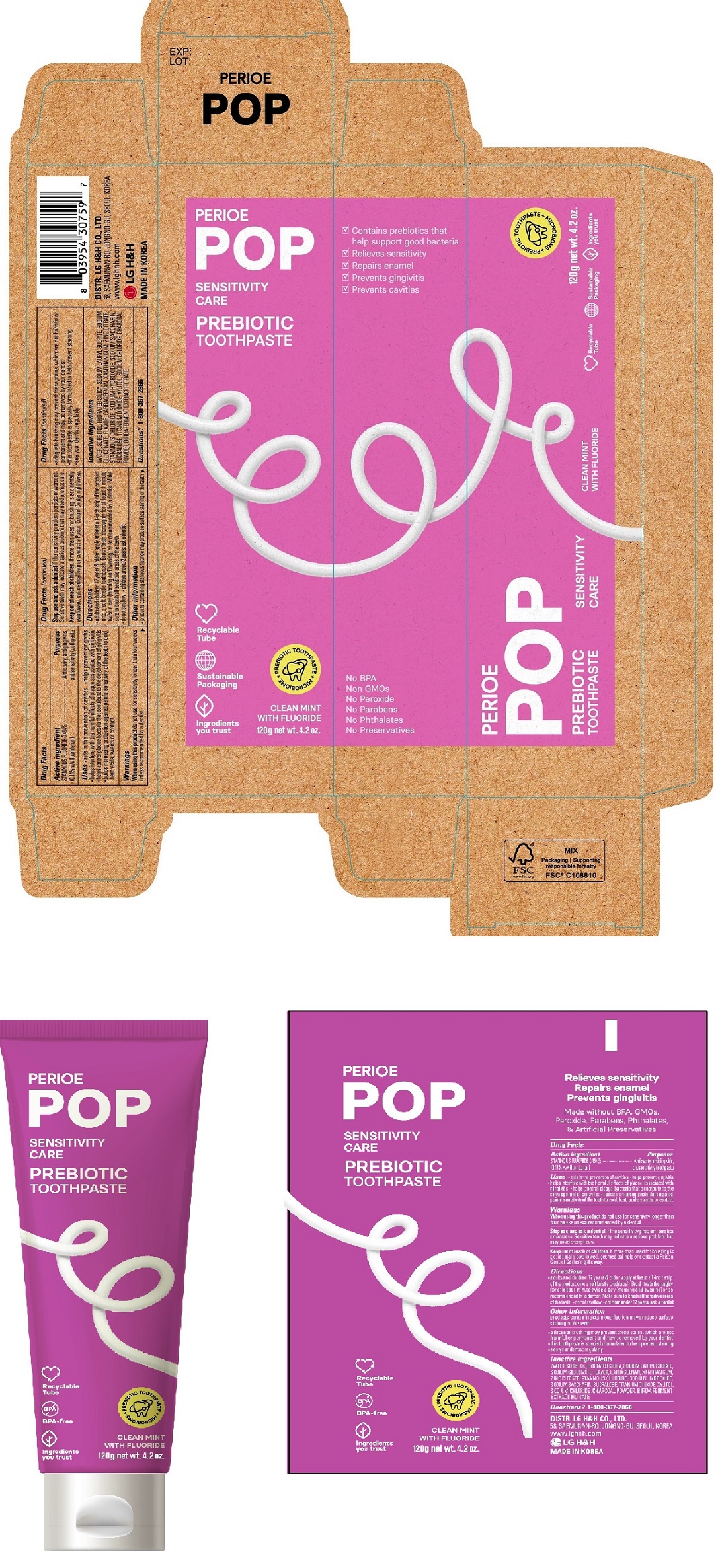 DRUG LABEL: PERIOE POP Sensitivity Care Prebiotic
NDC: 43136-601 | Form: PASTE, DENTIFRICE
Manufacturer: Tai Guk Pharm. Co., Ltd.
Category: otc | Type: HUMAN OTC DRUG LABEL
Date: 20250101

ACTIVE INGREDIENTS: STANNOUS FLUORIDE 1.4 mg/1 g
INACTIVE INGREDIENTS: SUCRALOSE; HYDRATED SILICA; SORBITOL; WATER; SODIUM GLUCONATE; CARRAGEENAN; SODIUM LAURYL SULFATE; XYLITOL; SACCHARIN SODIUM; STANNOUS CHLORIDE; TITANIUM DIOXIDE; ZINC CITRATE; SODIUM CHLORIDE; SODIUM HYDROXIDE; XANTHAN GUM; ACTIVATED CHARCOAL

PERIOE POP Sensitivity Care Prebiotic Toothpaste Clean Mint 120 g

Drug Facts

Active Ingredient

STANNOUS FLUORIDE 0.454% (0.14% w/v fluoride ion)

Purposes

Anticavity, antigingivitis, antisensitivity toothpaste

Uses

- aids in the prevention of cavities
- helps prevent gingivitis
- helps interfere with the harmful effects of plaque associated with gingivitis
- helps control plaque bacteria that contribute to the develpment of gingivitis
- builds increasing protection against painful sensitivity of the teeth to cold, heat, acids, sweets or contact

Warnings

When using this product

When using this productdo not use for sensitivity longer than four weeks unless recommended by a dentist.

Stop use and ask a dentist

Stop use and ask a dentistif the sensitivity problem persits or worsens. Sensitive teeth may indicate a serious problem that may need prompt care.

Keep out of reach of children.If more than used for brushing is accidentally swallowed, get medical help or contact a Poison Control Center right away.

Directions

- adults and children 12 years & older: apply at least a 1-inch strip of the product onto a soft bristle toothbrush. Brush teeth thoroughly for at least 1 minute twice a day (morning and evening) or as recommended by a dentist. Make sure to brush all sensitive areas of the teeth.
- do not swallow
- children under 12 years: ask a dentist.

Other information

- products containing stannous fluoride may produce surface staining of the teeth
- adequate brushing may prevent these stains which are not harmful or permanent and may be removed by your dentist
- this toothpaste is specially formulated to help prevent staining
- see your dentist regularly

Inactive Ingredients

WATER, SORBITOL, HYDRATED SILICA, SODIUM LAURYL SULFATE, SODIUM GLUCONATE, FLAVOR, CARRAGEENAN, XANTHAN GUM, ZINC CITRATE, STANNOUS CHLORIDE, SODIUM HYDROXIDE, SODIUM SACCHARIN, SUCRALOSE, TITANIUM DIOXIDE, XYLITOL, SODIUM CHLORIDE, CHARCOAL POWDER, BIFIDA FERMENT EXTRACT FILTRATE

Questions?

1-800-367-2866

Distributed by

DISTR. LG H&H CO., LTD.
58, SAEMUNAN-RO, JONGNO-GU, SEOUL, KOREA
www.lghnh.com
LG H&H
MADE IN KOREA

Principal Display Panel - 120 g Tube Carton

PERIOE

POP

SENSITIVITY
CARE

PREBIOTIC
TOOTHPASTE

CLEAN MINT
WITH FLUORIDE

120g net wt. 4.2 oz.